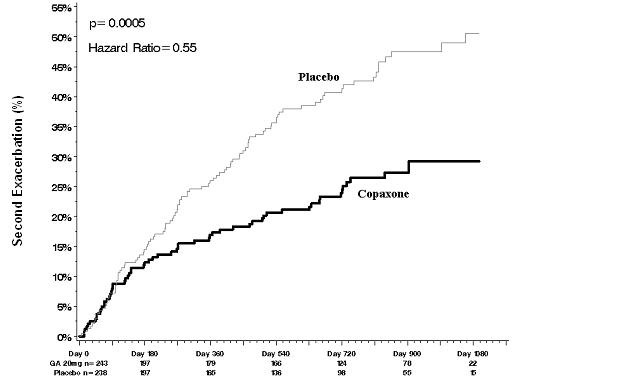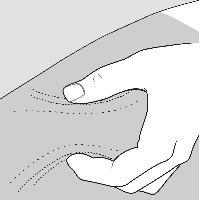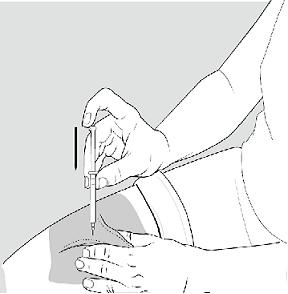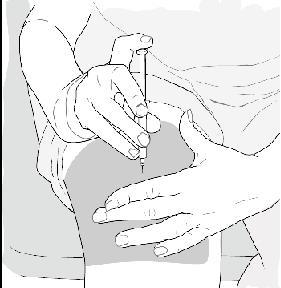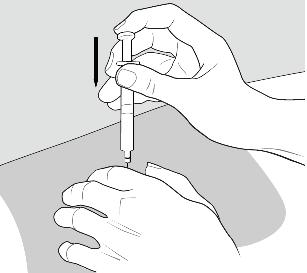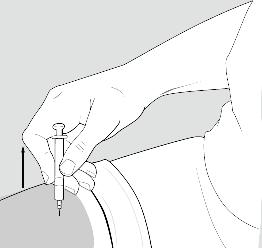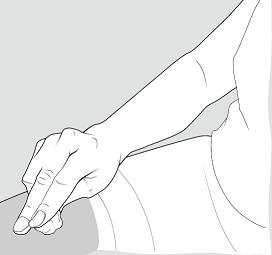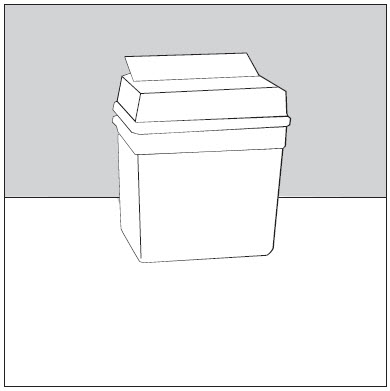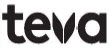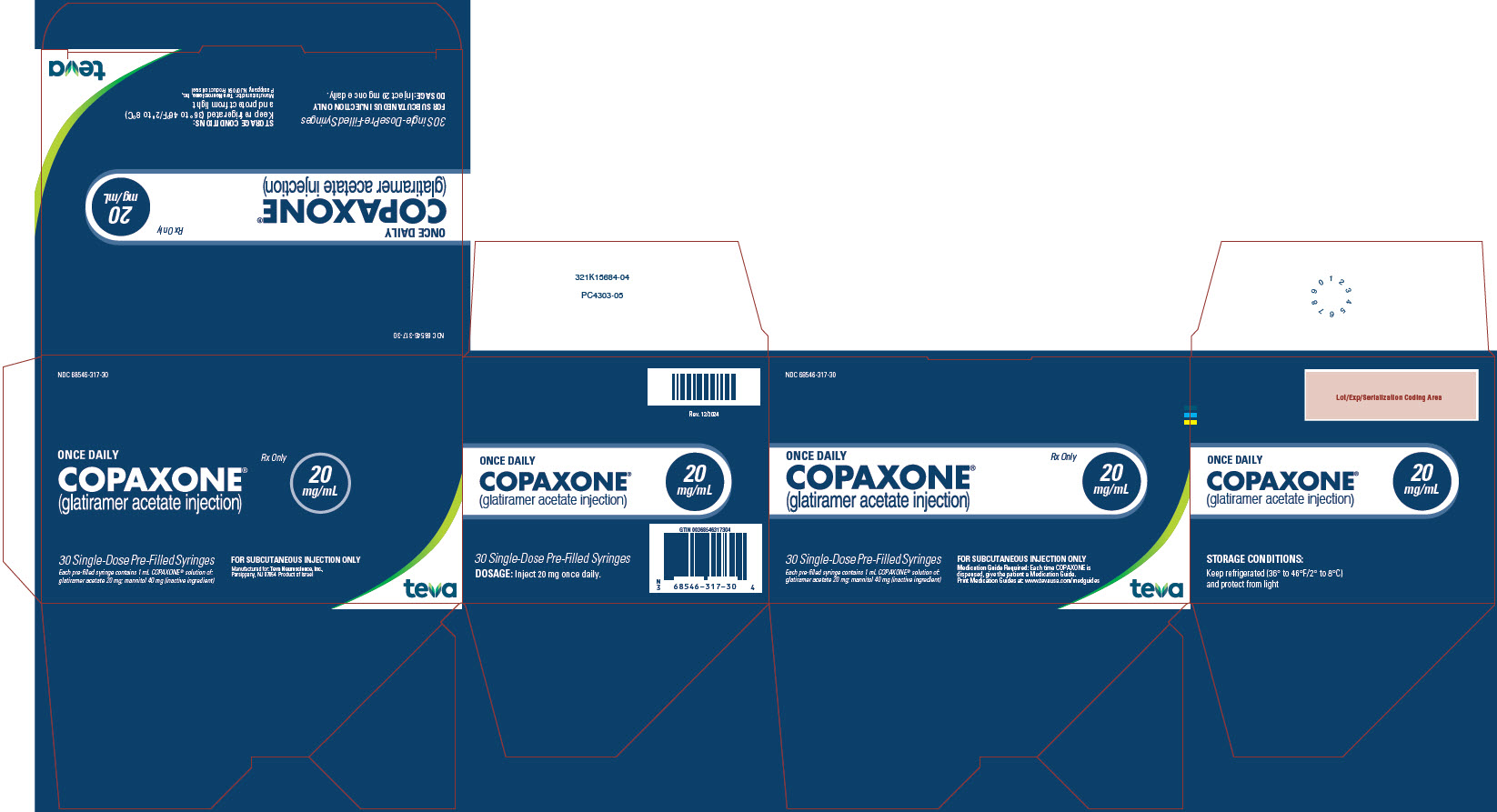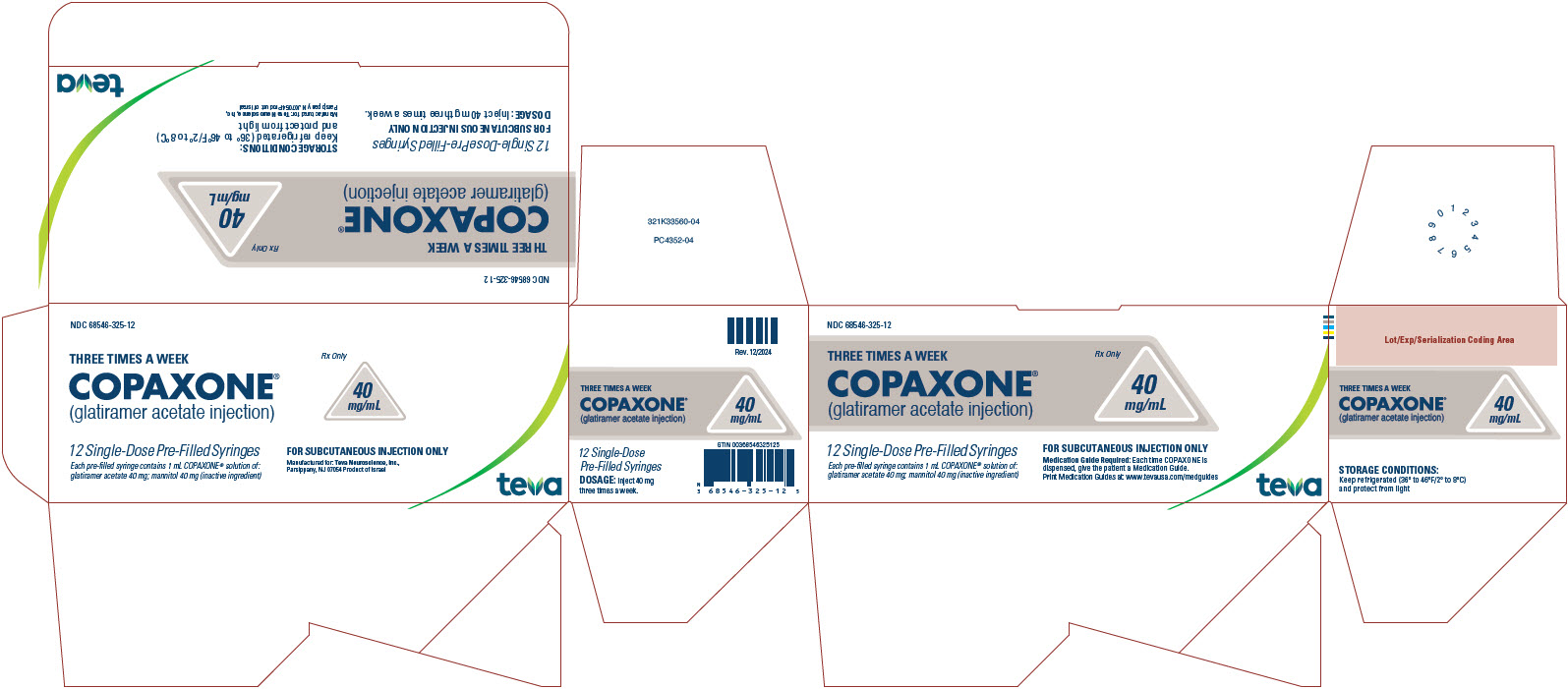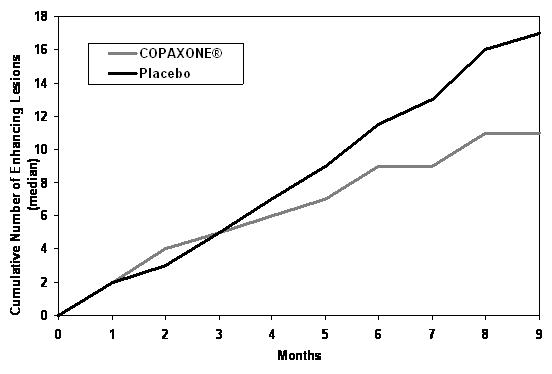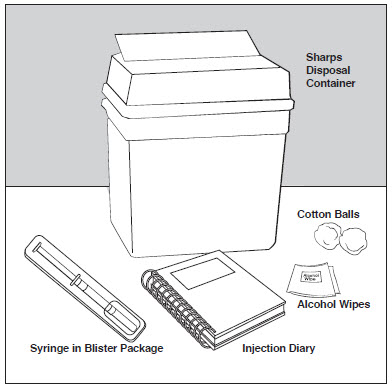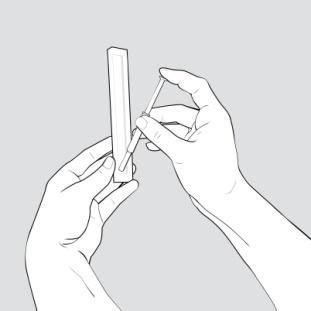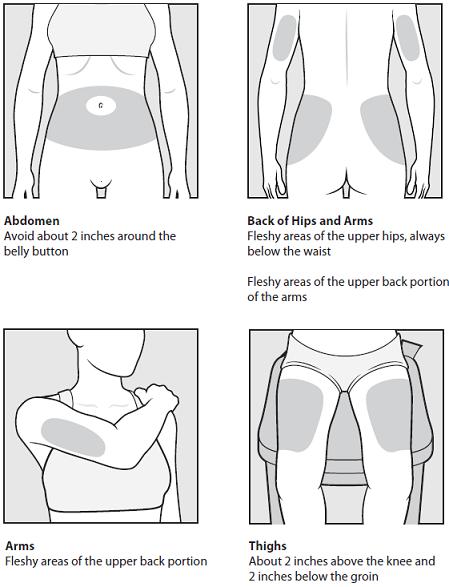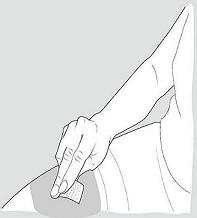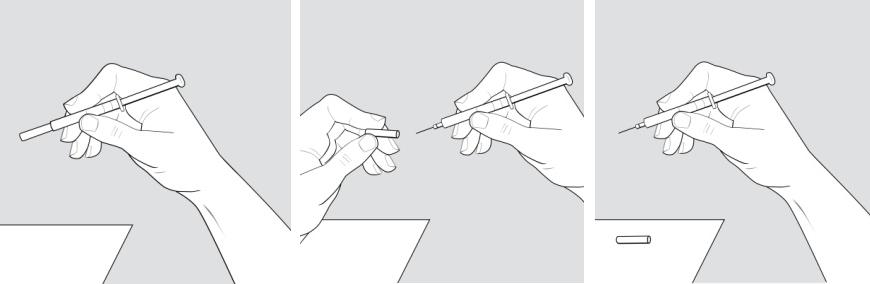 DRUG LABEL: Copaxone
NDC: 68546-317 | Form: INJECTION, SOLUTION
Manufacturer: Teva Neuroscience, Inc.
Category: prescription | Type: HUMAN PRESCRIPTION DRUG LABEL
Date: 20250131

ACTIVE INGREDIENTS: GLATIRAMER ACETATE 20 mg/1 mL
INACTIVE INGREDIENTS: MANNITOL 40 mg/1 mL

HIGHLIGHTS OF PRESCRIBING INFORMATION

These highlights do not include all the information needed to use COPAXONE® safely and effectively. See full prescribing information for COPAXONE.
COPAXONE (glatiramer acetate injection), for subcutaneous use
Initial U.S. Approval: 1996

RECENT MAJOR CHANGES

Boxed Warning 1/2025

Contraindications (4) 1/2025

Warnings and Precautions (5.1, 5.2, 5.5) 1/2025

WARNING: ANAPHYLACTIC REACTIONS

See full prescribing information for complete boxed warning.

Life-threatening and fatal anaphylaxis, which can occur at any time following initiation of therapy (from as early as after the first dose, up to years after initiation of treatment), has been reported in patients receiving COPAXONE.

- Make patients aware of the symptoms of anaphylaxis, which may overlap with those of an immediate post-injection reaction. Prompt identification of anaphylaxis is important to avoid a delay in treatment (5.1).
- COPAXONE is contraindicated in patients with a history of hypersensitivity reactions to COPAXONE, including anaphylaxis (4).

1 INDICATIONS AND USAGE

COPAXONE is indicated for the treatment of relapsing forms of multiple sclerosis (MS), to include clinically isolated syndrome, relapsing-remitting disease, and active secondary progressive disease, in adults (1).

2 DOSAGE AND ADMINISTRATION

- For subcutaneous injection only; doses are not interchangeable (2.1)
- COPAXONE 20 mg/mL per day (2.1)
- COPAXONE 40 mg/mL three times per week (2.1)
- Before use, allow the solution to warm to room temperature (2.2)

3 DOSAGE FORMS AND STRENGTHS

- Injection: 20 mg/mL in a single-dose prefilled syringe with a white plunger (3)
- Injection: 40 mg/mL in a single-dose, prefilled syringe with a blue plunger (3)

4 CONTRAINDICATIONS

Known hypersensitivity to glatiramer acetate or mannitol (4)

5 WARNINGS AND PRECAUTIONS

- Immediate Post-Injection Reaction (flushing, chest pain, palpitations, tachycardia, anxiety, dyspnea, throat constriction, and/or urticaria), may occur within seconds to minutes after injection and are generally transient and self-limiting (5.2)
- Chest pain, usually transient (5.3)
- Lipoatrophy and skin necrosis may occur. Instruct patients in proper injection technique and to rotate injection sites (5.4)
- COPAXONE can modify immune response (5.5)
- Hepatic Injury: if signs or symptoms of hepatic dysfunction occur, consider discontinuing COPAXONE (5.6)
- Glatiramer Acetate Products and Administration Errors: Using an optional autoinjector that is not compatible for use with TEVA’s COPAXONE may increase the risk for medication errors, such as dose omission or administration of a partial dose. (5.7)

6 ADVERSE REACTIONS

- In controlled studies of COPAXONE 20 mg/mL, most common adverse reactions (≥10% and ≥1.5 times higher than placebo) were: injection site reactions, vasodilatation, rash, dyspnea, and chest pain (6.1)
- In a controlled study of COPAXONE 40 mg/mL, most common adverse reactions (≥10% and ≥1.5 times higher than placebo) were: injection site reactions (6.1)

To report SUSPECTED ADVERSE REACTIONS, contact Teva Pharmaceuticals at 1-888-483-8279 or FDA at 1-800-FDA-1088 or www.fda.gov/medwatch.

FULL PRESCRIBING INFORMATION

WARNING: ANAPHYLACTIC REACTIONS

Cases of life-threatening and fatal anaphylaxis have been reported with COPAXONE. Anaphylaxis can occur at any time following initiation of therapy, from as early as after the first dose, up to years following initiation of therapy.

- Make patients aware of the symptoms of anaphylaxis, which may overlap with those of an immediate post-injection reaction; instruct them to seek immediate medical care should these symptoms occur. Prompt identification of anaphylaxis is important to avoid a delay in treatment [see Warnings and Precautions (5.1)].
- COPAXONE is contraindicated in patients with a history of hypersensitivity reactions to COPAXONE, including anaphylaxis. If an anaphylactic reaction occurs, treatment with COPAXONE must be immediately discontinued. Unless a clear alternative etiology is identified, COPAXONE must be permanently discontinued [see Contraindications (4) and Warnings and Precautions (5.1)].

1 INDICATIONS AND USAGE

COPAXONE is indicated for the treatment of relapsing forms of multiple sclerosis (MS), to include clinically isolated syndrome, relapsing-remitting disease, and active secondary progressive disease, in adults.

2 DOSAGE AND ADMINISTRATION

2.1 Recommended Dose

COPAXONE is for subcutaneous use only [see Dosage and Administration (2.2)]. Do not administer intravenously. The dosing schedule depends on the product strength that is selected. The recommended doses are:

- COPAXONE 20 mg per mL: administer once per day
  or
- COPAXONE 40 mg per mL: administer three times per week and at least 48 hours apart

COPAXONE 20 mg per mL and COPAXONE 40 mg per mL are not interchangeable.

2.2 Instructions for Use

Remove one blister-packaged prefilled syringe from the refrigerated carton. Let the prefilled syringe stand at room temperature for 20 minutes to allow the solution to warm to room temperature. Visually inspect the syringe for particulate matter and discoloration prior to administration. The solution in the syringe should appear clear, colorless to slightly yellow. If particulate matter or discoloration is observed, discard the syringe.

Areas for subcutaneous self-injection include arms, abdomen, hips, and thighs. The prefilled syringe is for single use only. Discard unused portions.

Using an autoinjector that is not compatible for use with TEVA’s COPAXONE may increase the risk for medication errors, such as dose omission or administration of a partial dose [see Warnings and Precautions (5.7)].

3 DOSAGE FORMS AND STRENGTHS

- Injection: 20 mg per mL in a single-dose, prefilled syringe with a white plunger. For subcutaneous use only.
- Injection: 40 mg per mL in a single-dose, prefilled syringe with a blue plunger. For subcutaneous use only.

4 CONTRAINDICATIONS

COPAXONE is contraindicated in patients with known hypersensitivity to glatiramer acetate or mannitol. Reactions have included anaphylaxis [see Warnings and Precautions (5.1)].

5 WARNINGS AND PRECAUTIONS

5.1 Anaphylactic Reactions

Life-threatening and fatal anaphylaxis has been reported with COPAXONE [see Adverse Reactions (6.2)]. COPAXONE is contraindicated in patients with a history of hypersensitivity reactions to COPAXONE, including anaphylaxis [see Contraindications (4)]. Anaphylaxis can occur at any time following initiation of COPAXONE therapy, from as early as after the first dose, up to years after initiation of treatment. Anaphylaxis occurred within an hour of a COPAXONE injection in most of the reported cases.

Some signs and symptoms of anaphylactic reactions may overlap with those of immediate post-injection reactions [see Warnings and Precautions (5.2)]. All patients receiving treatment with COPAXONE and caregivers should be informed about the signs and symptoms of anaphylactic reactions, and that they must seek immediate emergency medical care in case of experiencing such symptoms. If an anaphylactic reaction occurs, treatment with COPAXONE must be immediately discontinued. Unless a clear alternative etiology is identified, COPAXONE must be permanently discontinued [see Contraindications (4)].

5.2 Immediate Post-Injection Reaction

Approximately 16% of patients exposed to COPAXONE 20 mg per mL in the 5 placebo-controlled trials compared to 4% of those on placebo, and approximately 2% of patients exposed to COPAXONE 40 mg per mL in a placebo-controlled trial compared to none on placebo, experienced a constellation of symptoms that may occur immediately (within seconds to minutes, with the majority of symptoms observed within 1 hour) after injection and included at least two of the following: flushing, chest pain, palpitations, tachycardia, anxiety, dyspnea, constriction of the throat, and urticaria. These events are termed immediate post-injection reactions.

The symptoms of an immediate post-injection reaction may overlap with those of anaphylaxis; prompt identification of anaphylaxis is important to avoid a delay in treatment. In general, symptoms of an immediate post-injection reaction have onset several months after the initiation of treatment, although they may occur earlier, and a given patient may experience one or several episodes of these symptoms. Whether or not any of these symptoms actually represent a specific syndrome is uncertain. Typically, the symptoms were transient and self-limited and did not require treatment; however, there have been reports of patients with similar symptoms who developed fatal anaphylaxis and/or received emergency medical care. Whether an immunologic or nonimmunologic mechanism mediates these episodes, or whether several similar episodes seen in a given patient have identical mechanisms, is unknown.

5.3 Chest Pain

Approximately 13% of COPAXONE 20 mg per mL patients in the 5 placebo-controlled studies compared to 6% of placebo patients, and approximately 2% of patients exposed to COPAXONE 40 mg per mL in a placebo-controlled trial compared to 1% of placebo patients, experienced at least one episode of transient chest pain. While some of these episodes occurred in the context of the Immediate Post-Injection Reaction described above, many did not. The temporal relationship of this chest pain to an injection was not always known. The pain was usually transient, often unassociated with other symptoms, and appeared to have no clinical sequelae. Some patients experienced more than one such episode, and episodes usually began at least 1 month after the initiation of treatment. The pathogenesis of this symptom is unknown.

5.4 Lipoatrophy and Skin Necrosis

At injection sites, localized lipoatrophy and, rarely, injection site skin necrosis may occur. Lipoatrophy occurred in approximately 2% of patients exposed to COPAXONE 20 mg per mL in the 5 placebo-controlled trials compared to none on placebo, and 0.5% of patients exposed to COPAXONE 40 mg per mL in a single placebo-controlled trial and none on placebo. Skin necrosis has only been observed in the postmarketing setting. Lipoatrophy may occur at various times after treatment onset (sometimes after several months) and is thought to be permanent. There is no known therapy for lipoatrophy. To assist in possibly minimizing these events, the patient should be advised to follow proper injection technique and to rotate injection sites with each injection.

5.5 Potential Effects on Immune Response

Because COPAXONE can modify immune response, it may interfere with immune functions. For example, treatment with COPAXONE may interfere with the recognition of foreign antigens in a way that would undermine the body's tumor surveillance and its defenses against infection. There is no evidence that COPAXONE does this, but there has not been a systematic evaluation of this risk. Because COPAXONE is an antigenic material, it is possible that its use may lead to the induction of host responses that are untoward, but systematic surveillance for these effects has not been undertaken.

Although COPAXONE is intended to minimize the autoimmune response to myelin, there is the possibility that continued alteration of cellular immunity due to chronic treatment with COPAXONE may result in untoward effects.

Glatiramer acetate-reactive antibodies are formed in most patients receiving glatiramer acetate. Studies in both the rat and monkey have suggested that immune complexes are deposited in the renal glomeruli. Furthermore, in a controlled trial of 125 RRMS patients given COPAXONE 20 mg per mL, subcutaneously every day for 2 years, serum IgG levels reached at least 3 times baseline values in 80% of patients by 3 months of initiation of treatment. By 12 months of treatment, however, 30% of patients still had IgG levels at least 3 times baseline values, and 90% had levels above baseline by 12 months. The antibodies are exclusively of the IgG subtype and predominantly of the IgG-1 subtype. No IgE type antibodies could be detected in any of the 94 sera tested; nevertheless, anaphylaxis can be associated with the administration of most any foreign substance and has been reported with COPAXONE [see Warnings and Precautions (5.1)].

5.6 Hepatic Injury

Cases of hepatic injury, some severe, including liver failure and hepatitis with jaundice, have been reported with COPAXONE. Hepatic injury has occurred from days to years after initiating treatment with COPAXONE. If signs or symptoms of liver dysfunction occur, consider discontinuation of COPAXONE.

5.7 Glatiramer Acetate Products and Administration Errors

Medication errors have occurred when glatiramer acetate products are administered with incompatible autoinjectors. Some glatiramer acetate products can be administered by an optional compatible autoinjector, should one be available; however, not all glatiramer acetate products have a marketed optional compatible autoinjector for administration [see Dosage and Administration (2.2) and How Supplied/Storage and Handling (16)].

Using an optional autoinjector that is not compatible for use with TEVA’s COPAXONE may increase the risk for medication errors, such as dose omission or administration of a partial dose.

If using an optional autoinjector for administration, ensure the device is compatible for use with the specific glatiramer acetate product by referring to the autoinjector labeling. The availability of compatible autoinjectors for each glatiramer acetate product may change with time.

6 ADVERSE REACTIONS

The following serious adverse reactions are described elsewhere in the labeling:

- Anaphylactic Reactions [see Warnings and Precautions (5.1)]
- Immediate Post-Injection Reaction [see Warnings and Precautions (5.2)]
- Chest Pain [see Warnings and Precautions (5.3)]
- Lipoatrophy and Skin Necrosis [see Warnings and Precautions (5.4)]
- Potential Effects on Immune Response [see Warnings and Precautions (5.5)]
- Hepatic Injury [see Warnings and Precautions (5.6)]

6.1 Clinical Trials Experience

Because clinical trials are conducted under widely varying conditions, adverse reaction rates observed in the clinical trials of a drug cannot be directly compared to rates in the clinical trials of another drug and may not reflect the rates observed in practice.

Incidence in Controlled Clinical Trials

COPAXONE 20 mg per mL per day

Among 563 patients treated with COPAXONE in blinded placebo-controlled trials, approximately 5% of the subjects discontinued treatment because of an adverse reaction. The adverse reactions most commonly associated with discontinuation were: injection site reactions, dyspnea, urticaria, vasodilatation, and hypersensitivity. The most common adverse reactions were: injection site reactions, vasodilatation, rash, dyspnea, and chest pain.

Table 1 lists signs and symptoms that occurred in at least 2% of patients treated with COPAXONE 20 mg per mL in the placebo-controlled trials. These signs and symptoms were numerically more common in patients treated with COPAXONE than in patients treated with placebo. Adverse reactions were usually mild in intensity.

Table 1: Adverse Reactions in Controlled Clinical Trials with an Incidence ≥2% of Patients and More Frequent with COPAXONE (20 mg per mL Daily) than with Placebo
 |  | COPAXONE; 20 mg/mL (n=563); % | Placebo; (n=564); %
Blood And Lymphatic System Disorders | Lymphadenopathy | 7 | 3
Cardiac Disorders | Palpitations | 9 | 4
Cardiac Disorders | Tachycardia | 5 | 2
Eye Disorders | Eye Disorder | 3 | 1
Eye Disorders | Diplopia | 3 | 2
Gastrointestinal Disorders | Nausea | 15 | 11
Gastrointestinal Disorders | Vomiting | 7 | 4
Gastrointestinal Disorders | Dysphagia | 2 | 1
General Disorders And Administration Site Conditions | Injection Site Erythema | 43 | 10
General Disorders And Administration Site Conditions | Injection Site Pain | 40 | 20
General Disorders And Administration Site Conditions | Injection Site Pruritus | 27 | 4
General Disorders And Administration Site Conditions | Injection Site Mass | 26 | 6
General Disorders And Administration Site Conditions | Asthenia | 22 | 21
General Disorders And Administration Site Conditions | Pain | 20 | 17
General Disorders And Administration Site Conditions | Injection Site Edema | 19 | 4
General Disorders And Administration Site Conditions | Chest Pain | 13 | 6
General Disorders And Administration Site Conditions | Injection Site Inflammation | 9 | 1
General Disorders And Administration Site Conditions | Edema | 8 | 2
General Disorders And Administration Site Conditions | Injection Site Reaction | 8 | 1
General Disorders And Administration Site Conditions | Pyrexia | 6 | 5
General Disorders And Administration Site Conditions | Injection Site Hypersensitivity | 4 | 0
General Disorders And Administration Site Conditions | Local Reaction | 3 | 1
General Disorders And Administration Site Conditions | Chills | 3 | 1
General Disorders And Administration Site Conditions | Face Edema | 3 | 1
General Disorders And Administration Site Conditions | Edema Peripheral | 3 | 2
General Disorders And Administration Site Conditions | Injection Site Fibrosis | 2 | 1
General Disorders And Administration Site Conditions | Injection Site Atrophy* | 2 | 0
Immune System Disorders | Hypersensitivity | 3 | 2
Infections And Infestations | Infection | 30 | 28
Infections And Infestations | Influenza | 14 | 13
Infections And Infestations | Rhinitis | 7 | 5
Infections And Infestations | Bronchitis | 6 | 5
Infections And Infestations | Gastroenteritis | 6 | 4
Infections And Infestations | Vaginal Candidiasis | 4 | 2
Metabolism And Nutrition Disorders | Weight Increased | 3 | 1
Musculoskeletal And Connective Tissue Disorders | Back Pain | 12 | 10
Neoplasms Benign, Malignant And Unspecified (Incl Cysts And Polyps) | Benign Neoplasm of Skin | 2 | 1
Nervous System Disorders | Tremor | 4 | 2
Nervous System Disorders | Migraine | 4 | 2
Nervous System Disorders | Syncope | 3 | 2
Nervous System Disorders | Speech Disorder | 2 | 1
Psychiatric Disorders | Anxiety | 13 | 10
Psychiatric Disorders | Nervousness | 2 | 1
Renal And Urinary Disorders | Micturition Urgency | 5 | 4
Respiratory, Thoracic And Mediastinal Disorders | Dyspnea | 14 | 4
Respiratory, Thoracic And Mediastinal Disorders | Cough | 6 | 5
Respiratory, Thoracic And Mediastinal Disorders | Laryngospasm | 2 | 1
Skin And Subcutaneous Tissue Disorders | Rash | 19 | 11
Skin And Subcutaneous Tissue Disorders | Hyperhidrosis | 7 | 5
Skin And Subcutaneous Tissue Disorders | Pruritus | 5 | 4
Skin And Subcutaneous Tissue Disorders | Urticaria | 3 | 1
Skin And Subcutaneous Tissue Disorders | Skin Disorder | 3 | 1
Vascular Disorders | Vasodilatation | 20 | 5

*Injection site atrophy comprises terms relating to localized lipoatrophy at injection site

Adverse reactions which occurred only in 4 to 5 more subjects in the COPAXONE group than in the placebo group (less than 1% difference), but for which a relationship to COPAXONE could not be excluded, were arthralgia and herpes simplex.

Laboratory analyses were performed on all patients participating in the clinical program for COPAXONE. Clinically-significant laboratory values for hematology, chemistry, and urinalysis were similar for both COPAXONE and placebo groups in blinded clinical trials. In controlled trials one patient discontinued treatment due to thrombocytopenia (16 x10^9/L), which resolved after discontinuation of treatment.

Data on adverse reactions occurring in the controlled clinical trials of COPAXONE 20 mg per mL were analyzed to evaluate differences based on sex. No clinically-significant differences were identified. Ninety-six percent of patients in these clinical trials were Caucasian. The majority of patients treated with COPAXONE were between the ages of 18 and 45. Consequently, data are inadequate to perform an analysis of the adverse reaction incidence related to clinically-relevant age subgroups.

Other Adverse Reactions

In the paragraphs that follow, the frequencies of less commonly reported adverse clinical reactions are presented. Because the reports include reactions observed in open and uncontrolled premarketing studies (n= 979), the role of COPAXONE in their causation cannot be reliably determined. Furthermore, variability associated with adverse reaction reporting, the terminology used to describe adverse reactions, etc., limit the value of the quantitative frequency estimates provided. Reaction frequencies are calculated as the number of patients who used COPAXONE and reported a reaction divided by the total number of patients exposed to COPAXONE. All reported reactions are included except those already listed in the previous table, those too general to be informative, and those not reasonably associated with the use of the drug. Reactions are further classified within body system categories and enumerated in order of decreasing frequency using the following definitions: Frequent adverse reactions are defined as those occurring in at least 1/100 patients and infrequent adverse reactions are those occurring in 1/100 to 1/1,000 patients.

Body as a Whole:

Frequent: Abscess

Infrequent: Injection site hematoma, moon face, cellulitis, hernia, injection site abscess, serum sickness, suicide attempt, injection site hypertrophy, injection site melanosis, lipoma, and photosensitivity reaction.

Cardiovascular:

Frequent: Hypertension.

Infrequent: Hypotension, midsystolic click, systolic murmur, atrial fibrillation, bradycardia, fourth heart sound, postural hypotension, and varicose veins.

Digestive:

Infrequent: Dry mouth, stomatitis, burning sensation on tongue, cholecystitis, colitis, esophageal ulcer, esophagitis, gastrointestinal carcinoma, gum hemorrhage, hepatomegaly, increased appetite, melena, mouth ulceration, pancreas disorder, pancreatitis, rectal hemorrhage, tenesmus, tongue discoloration, and duodenal ulcer.

Endocrine:

Infrequent: Goiter, hyperthyroidism, and hypothyroidism.

Gastrointestinal:

Frequent: Bowel urgency, oral moniliasis, salivary gland enlargement, tooth caries, and ulcerative stomatitis.

Hemic and Lymphatic:

Infrequent: Leukopenia, anemia, cyanosis, eosinophilia, hematemesis, lymphedema, pancytopenia, and splenomegaly.

Metabolic and Nutritional:

Infrequent: Weight loss, alcohol intolerance, Cushing’s syndrome, gout, abnormal healing, and xanthoma.

Musculoskeletal:

Infrequent: Arthritis, muscle atrophy, bone pain, bursitis, kidney pain, muscle disorder, myopathy, osteomyelitis, tendon pain, and tenosynovitis.

Nervous:

Frequent: Abnormal dreams, emotional lability, and stupor.

Infrequent: Aphasia, ataxia, convulsion, circumoral paresthesia, depersonalization, hallucinations, hostility, hypokinesia, coma, concentration disorder, facial paralysis, decreased libido, manic reaction, memory impairment, myoclonus, neuralgia, paranoid reaction, paraplegia, psychotic depression, and transient stupor.

Respiratory:

Frequent: Hyperventilation and hay fever.

Infrequent: Asthma, pneumonia, epistaxis, hypoventilation, and voice alteration.

Skin and Appendages:

Frequent: Eczema, herpes zoster, pustular rash, skin atrophy, and warts.

Infrequent: Dry skin, skin hypertrophy, dermatitis, furunculosis, psoriasis, angioedema, contact dermatitis, erythema nodosum, fungal dermatitis, maculopapular rash, pigmentation, benign skin neoplasm, skin carcinoma, skin striae, and vesiculobullous rash.

Special Senses:

Frequent: Visual field defect.

Infrequent: Dry eyes, otitis externa, ptosis, cataract, corneal ulcer, mydriasis, optic neuritis, photophobia, and taste loss.

Urogenital:

Frequent: Amenorrhea, hematuria, impotence, menorrhagia, suspicious papanicolaou smear, urinary frequency, and vaginal hemorrhage.

Infrequent: Vaginitis, flank pain (kidney), breast engorgement, breast enlargement, carcinoma in situ cervix, fibrocystic breast, kidney calculus, nocturia, ovarian cyst, priapism, pyelonephritis, abnormal sexual function, and urethritis.

COPAXONE 40 mg per mL three times per week

Among 943 patients treated with COPAXONE 40 mg per mL three times per week in a blinded, placebo-controlled trial, approximately 3% of the subjects discontinued treatment because of an adverse reaction. The most common adverse reactions were injection site reactions, which were also the most common cause of discontinuation.

Table 2 lists signs and symptoms that occurred in at least 2% of patients treated with COPAXONE 40 mg per mL in the blinded, placebo-controlled trial. These signs and symptoms were numerically more common in patients treated with COPAXONE 40 mg per mL than in patients treated with placebo. Adverse reactions were usually mild in intensity.

Table 2: Adverse Reactions in a Controlled Clinical Trial with an Incidence ≥2% of Patients and More Frequent with COPAXONE (40 mg per mL Three Times per Week) than with Placebo
 |  | COPAXONE; 40 mg/mL; (n=943); % | Placebo; (n=461); %
General Disorders And Administration Site Conditions | Injection Site Erythema | 22 | 2
General Disorders And Administration Site Conditions | Injection Site Pain | 10 | 2
General Disorders And Administration Site Conditions | Injection Site Mass | 6 | 0
General Disorders And Administration Site Conditions | Injection Site Pruritus | 6 | 0
General Disorders And Administration Site Conditions | Injection Site Edema | 6 | 0
General Disorders And Administration Site Conditions | Pyrexia | 3 | 2
General Disorders And Administration Site Conditions | Influenza-like Illness | 3 | 2
General Disorders And Administration Site Conditions | Injection Site Inflammation | 2 | 0
General Disorders And Administration Site Conditions | Chills | 2 | 0
General Disorders And Administration Site Conditions | Chest Pain | 2 | 1
Infections And Infestations | Nasopharyngitis | 11 | 9
Infections And Infestations | Respiratory Tract Infection Viral | 3 | 2
Respiratory, Thoracic and Mediastinal Disorders | Dyspnea | 3 | 0
Vascular Disorders | Vasodilatation | 3 | 0
Gastrointestinal Disorders | Nausea | 2 | 1
Skin And Subcutaneous Tissue Disorders | Erythema | 2 | 0
Skin And Subcutaneous Tissue Disorders | Rash | 2 | 1

No new adverse reactions appeared in subjects treated with COPAXONE 40 mg per mL three times per week as compared to subjects treated with COPAXONE 20 mg per mL per day in clinical trials and during postmarketing experience. Data on adverse reactions occurring in the controlled clinical trial of COPAXONE 40 mg per mL were analyzed to evaluate differences based on sex. No clinically significant differences were identified. Ninety-eight percent of patients in this clinical trial were Caucasian and the majority were between the ages of 18 and 50. Consequently, data are inadequate to perform an analysis of the adverse reaction incidence related to clinically-relevant age groups.

6.2 Postmarketing Experience

The following adverse reactions have been identified during postapproval use of COPAXONE. Because these reactions are reported voluntarily from a population of uncertain size, it is not always possible to reliably estimate their frequency or establish a causal relationship to drug exposure.

Body as a Whole: sepsis; SLE syndrome; hydrocephalus; enlarged abdomen; allergic reaction

Cardiovascular System: thrombosis; peripheral vascular disease; pericardial effusion; myocardial infarct; deep thrombophlebitis; coronary occlusion; congestive heart failure; cardiomyopathy; cardiomegaly; arrhythmia; angina pectoris

Digestive System: tongue edema; stomach ulcer; hemorrhage; eructation

Hemic and Lymphatic System: thrombocytopenia; lymphoma-like reaction; acute leukemia

Hepatobiliary Disorders: cholelithiasis; liver function abnormality; cirrhosis of the liver; hepatitis; hepatic injury [see Warnings and Precautions (5.6)]

Immune System Disorders: hypersensitivity reactions (including anaphylactic reactions) [see Boxed Warning and Warnings and Precautions (5.1)].

Metabolic and Nutritional Disorders: hypercholesterolemia

Musculoskeletal System: rheumatoid arthritis; generalized spasm

Nervous System: myelitis; meningitis; CNS neoplasm; cerebrovascular accident; brain edema; abnormal dreams; aphasia; convulsion; neuralgia

Respiratory System: pulmonary embolus; pleural effusion; carcinoma of lung

Special Senses: glaucoma; blindness

Urogenital System: urogenital neoplasm; urine abnormality; ovarian carcinoma; nephrosis; kidney failure; breast carcinoma; bladder carcinoma; urinary frequency

8 USE IN SPECIFIC POPULATIONS

8.1 Pregnancy

Risk Summary

Available data from pharmacovigilance and published observational studies over decades of use with glatiramer acetate during pregnancy have not identified a drug-associated risk of major birth defects, miscarriage, or other adverse maternal or fetal outcomes (see Data). Administration of glatiramer acetate by subcutaneous injection to pregnant rats and rabbits resulted in no adverse effects on embryofetal or offspring development (see Data).

The background risk of major birth defects and miscarriage for the indicated population is unknown. All pregnancies have a background risk of birth defect, loss, or other outcomes. In the US general population, the estimated background risk of major birth defects and miscarriage in clinically recognized pregnancies is 2% to 4% and 15% to 20%, respectively.

Data

Human Data

Data from pharmacovigilance and published observational studies have not identified a drug-associated risk of major birth defects, miscarriage, or other adverse maternal or fetal outcomes when glatiramer acetate was used during pregnancy. However, the published comparative observational studies have methodological limitations, such as short exposure duration during pregnancy, confounding, selection bias, and exposure misclassification.

Animal Data

In rats or rabbits receiving glatiramer acetate by subcutaneous injection during the period of organogenesis, no adverse effects on embryofetal development were observed at doses up to 37.5 mg/kg/day (18 and 36 times, respectively, the therapeutic human dose of 20 mg/day on a mg/m^2 basis). In rats receiving subcutaneous glatiramer acetate at doses of up to 36 mg/kg from day 15 of pregnancy throughout lactation, no significant effects on delivery or on offspring growth and development were observed.

8.2 Lactation

Risk Summary

There are no data on the presence of glatiramer acetate in human milk. Based on the low systemic exposure because of substantial local hydrolysis of glatiramer acetate following subcutaneous administration, breastfeeding is not expected to result in clinically relevant exposure of the infant to the drug [see Clinical Pharmacology (12.3)]. There are no data on the effects of glatiramer acetate on milk production.

The developmental and health benefits of breastfeeding should be considered along with the mother’s clinical need for COPAXONE and any potential adverse effects on the breastfed infant from COPAXONE or from the underlying maternal condition.

8.4 Pediatric Use

The safety and effectiveness of COPAXONE have not been established in patients under 18 years of age.

8.5 Geriatric Use

COPAXONE has not been studied in elderly patients.

8.6 Use in Patients with Impaired Renal Function

The pharmacokinetics of glatiramer acetate in patients with impaired renal function have not been determined.

11 DESCRIPTION

Glatiramer acetate, the active ingredient of COPAXONE, consists of the acetate salts of synthetic polypeptides, containing four naturally occurring amino acids: L-glutamic acid, L-alanine, L-tyrosine, and L-lysine with an average molar fraction of 0.141, 0.427, 0.095, and 0.338, respectively. The average molecular weight of glatiramer acetate is 5,000 – 9,000 daltons. Glatiramer acetate is identified by specific antibodies.

Chemically, glatiramer acetate is designated L-glutamic acid polymer with L-alanine, L-lysine and L-tyrosine, acetate (salt). Its structural formula is:

(Glu, Ala, Lys, Tyr)x●xCH3COOH

(C5H9NO4●C3H7NO2●C6H14N2O2●C9H11NO3)x●xC2H4O2

CAS - 147245-92-9

COPAXONE is a clear, colorless to slightly yellow, sterile, nonpyrogenic solution for subcutaneous injection. Each 1 mL of COPAXONE solution contains 20 mg or 40 mg of glatiramer acetate and the following inactive ingredient: 40 mg of mannitol. The pH of the solutions is approximately 5.5 to 7.0. The biological activity of glatiramer acetate is determined by its ability to block the induction of experimental autoimmune encephalomyelitis (EAE) in mice.

12 CLINICAL PHARMACOLOGY

12.1 Mechanism of Action

The mechanism(s) by which glatiramer acetate exerts its effects in patients with MS are not fully understood. However, glatiramer acetate is thought to act by modifying immune processes that are believed to be responsible for the pathogenesis of MS. This hypothesis is supported by findings of studies that have been carried out to explore the pathogenesis of experimental autoimmune encephalomyelitis, a condition induced in animals through immunization against central nervous system derived material containing myelin and often used as an experimental animal model of MS. Studies in animals and in vitro systems suggest that upon its administration, glatiramer acetate-specific suppressor T-cells are induced and activated in the periphery.

Because glatiramer acetate can modify immune functions, concerns exist about its potential to alter naturally-occurring immune responses. There is no evidence that glatiramer acetate does this, but this has not been systematically evaluated [see Warnings and Precautions (5.5)].

12.3 Pharmacokinetics

Results obtained in pharmacokinetic studies performed in humans (healthy volunteers) and animals support that a substantial fraction of the therapeutic dose delivered to patients subcutaneously is hydrolyzed locally. Larger fragments of glatiramer acetate can be recognized by glatiramer acetate-reactive antibodies. Some fraction of the injected material, either intact or partially hydrolyzed, is presumed to enter the lymphatic circulation, enabling it to reach regional lymph nodes, and some may enter the systemic circulation intact.

13 NONCLINICAL TOXICOLOGY

13.1 Carcinogenesis, Mutagenesis, Impairment of Fertility

Carcinogenesis

In a 2-year carcinogenicity study, mice were administered up to 60 mg/kg/day glatiramer acetate by subcutaneous injection (up to 15 times the human therapeutic dose of 20 mg/day on a mg/m^2 basis). No increase in systemic neoplasms was observed. In males receiving the 60-mg/kg/day dose, there was an increased incidence of fibrosarcomas at the injection sites. These sarcomas were associated with skin damage precipitated by repetitive injections of an irritant over a limited skin area.

In a 2-year carcinogenicity study, rats were administered up to 30 mg/kg/day glatiramer acetate by subcutaneous injection (up to 15 times the human therapeutic dose on a mg/m^2 basis). No increase in neoplasms was observed.

Mutagenesis

Glatiramer acetate was not mutagenic in in vitro (Ames test, mouse lymphoma tk) assays. Glatiramer acetate was clastogenic in two separate in vitro chromosomal aberration assays in cultured human lymphocytes but not clastogenic in an in vivo mouse bone marrow micronucleus assay.

Impairment of Fertility

When glatiramer acetate was administered by subcutaneous injection prior to and during mating (males and females) and throughout gestation and lactation (females) at doses up to 36 mg/kg/day (18 times the human therapeutic dose on a mg/m^2 basis) no adverse effects were observed on reproductive or developmental parameters.

14 CLINICAL STUDIES

Evidence supporting the effectiveness of COPAXONE derives from five placebo-controlled trials, four of which used a COPAXONE dose of 20 mg per mL per day and one of which used a COPAXONE dose of 40 mg per mL three times per week.

COPAXONE 20 mg per mL per day

Study 1 was performed at a single center. Fifty patients were enrolled and randomized to receive daily doses of either COPAXONE, 20 mg per mL subcutaneously, or placebo (COPAXONE: n=25; placebo: n=25). Patients were diagnosed with RRMS by standard criteria, and had at least 2 exacerbations during the 2 years immediately preceding enrollment. Patients were ambulatory, as evidenced by a score of no more than 6 on the Kurtzke Disability Scale Score (DSS), a standard scale ranging from 0–Normal to 10–Death due to MS. A score of 6 is defined as one at which a patient is still ambulatory with assistance; a score of 7 means the patient must use a wheelchair.

Patients were examined every 3 months for 2 years, as well as within several days of a presumed exacerbation. To confirm an exacerbation, a blinded neurologist had to document objective neurologic signs, as well as document the existence of other criteria (e.g., the persistence of the neurological signs for at least 48 hours).

The protocol-specified primary outcome measure was the proportion of patients in each treatment group who remained exacerbation free for the 2 years of the trial, but two other important outcomes were also specified as endpoints: the frequency of attacks during the trial, and the change in the number of attacks compared with the number which occurred during the previous 2 years.

Table 3 presents the values of the three outcomes described above, as well as several protocol-specified secondary measures. These values are based on the intent-to-treat population (i.e., all patients who received at least 1 dose of treatment and who had at least 1 on-treatment assessment):

Table 3: Study 1 Efficacy Results
 | COPAXONE; 20 mg/mL; (n=25) | Placebo; (n=25) | P-Value
% Relapse-Free Patients | 14/25 (56%) | 7/25 (28%) | 0.085
Mean Relapse Frequency | 0.6/2 years | 2.4/2 years | 0.005
Reduction in Relapse Rate Compared to Prestudy | 3.2 | 1.6 | 0.025
Median Time to First Relapse (days) | >700 | 150 | 0.03
% of Progression-Free* Patients | 20/25 (80%) | 13/25 (52%) | 0.07

*Progression was defined as an increase of at least 1 point on the DSS, persisting for at least 3 consecutive months.

Study 2 was a multicenter trial of similar design which was performed in 11 US centers. A total of 251 patients (COPAXONE: n=125; placebo: n=126) were enrolled. The primary outcome measure was the Mean 2-Year Relapse Rate. Table 4 presents the values of this outcome for the intent-to-treat population, as well as several secondary measures:

Table 4: Study 2 Efficacy Results
 | COPAXONE; 20 mg/mL; (n=125) | Placebo; (n=126) | P-Value
Mean No. of Relapses | 1.19/2 years | 1.68 /2 years | 0.055
% Relapse-Free Patients | 42/125 (34%) | 34/126 (27%) | 0.25
Median Time to First Relapse (days) | 287 | 198 | 0.23
% of Progression-Free Patients | 98/125 (78%) | 95/126 (75%) | 0.48
Mean Change in DSS | -0.05 | +0.21 | 0.023

In both studies, COPAXONE exhibited a clear beneficial effect on relapse rate, and it is based on this evidence that COPAXONE is considered effective.

In Study 3, 481 patients who had recently (within 90 days) experienced an isolated demyelinating event and who had lesions typical of multiple sclerosis on brain MRI were randomized to receive either COPAXONE 20 mg per mL (n=243) or placebo (n=238). The primary outcome measure was time to development of a second exacerbation. Patients were followed for up to three years or until they reached the primary endpoint. Secondary outcomes were brain MRI measures, including number of new T2 lesions and T2 lesion volume.

Time to development of a second exacerbation was significantly delayed in patients treated with COPAXONE compared to placebo (Hazard Ratio = 0.55; 95% confidence interval 0.40 to 0.77; Figure 1). The Kaplan-Meier estimates of the percentage of patients developing a relapse within 36 months were 42.9% in the placebo group and 24.7% in the COPAXONE group.

Figure 1: Time to Second Exacerbation

Patients treated with COPAXONE demonstrated fewer new T2 lesions at the last observation (rate ratio 0.41; confidence interval 0.28 to 0.59; p < 0.0001). Additionally, baseline-adjusted T2 lesion volume at the last observation was lower for patients treated with COPAXONE (ratio of 0.89; confidence interval 0.84 to 0.94; p = 0.0001).

Study 4 was a multinational study in which MRI parameters were used both as primary and secondary endpoints. A total of 239 patients with RRMS (COPAXONE: n=119; and placebo: n=120) were randomized. Inclusion criteria were similar to those in the second study with the additional criterion that patients had to have at least one Gd-enhancing lesion on the screening MRI. The patients were treated in a double-blind manner for nine months, during which they underwent monthly MRI scanning. The primary endpoint for the double-blind phase was the total cumulative number of T1 Gd-enhancing lesions over the nine months. Table 5 summarizes the results for the primary outcome measure monitored during the trial for the intent-to-treat cohort.

Table 5: Study 4 MRI Results
 | COPAXONE; 20 mg/mL (n=119) | Placebo; (n=120) | P-Value
Medians of the Cumulative Number of T1 Gd-Enhancing Lesions | 11 | 17 | 0.0030

Figure 2 displays the results of the primary outcome on a monthly basis.

Figure 2: Median Cumulative Number of Gd-Enhancing Lesions

COPAXONE 40 mg per mL three times per week

Study 5 was a double-blind, placebo-controlled, multinational study with a total of 1404 patients with RRMS randomized in a 2:1 ratio to receive either COPAXONE 40 mg per mL (n=943) or placebo (n=461) three times a week for 12 months. Patients had a median of 2 relapses in the 2 years prior to screening and had not received any interferon-beta for at least 2 months prior to screening. Baseline EDSS scores ranged from 0 to 5.5 with a median of 2.5. Neurological evaluations were performed at baseline, every three months, and at unscheduled visits for suspected relapse or early termination. MRI was performed at baseline, months 6 and 12, or early termination. A total of 91% of those assigned to COPAXONE and 93% of those assigned to placebo completed treatment at 12 months.

The primary outcome measure was the total number of confirmed relapses (persistence of neurological symptoms for at least 48 hours confirmed on examination with objective signs). The effect of COPAXONE on several magnetic resonance imaging (MRI) variables, including number of new or enlarging T2 lesions and number of enhancing lesions on T1-weighted images, was also measured at months 6 and 12.

Table 6 presents the results for the intent-to-treat population.

Table 6: Study 5 Efficacy and MRI Results
 | COPAXONE; 40 mg/mL; (n=943) | Placebo; (n=461) | P-Value
Clinical Endpoints
Number of confirmed relapses during the 12-month placebo-controlled phase
Adjusted Mean Estimates; Relative risk reduction | 0.331; 34% | 0.505 | <0.0001
MRI Endpoints
Cumulative number of new or enlarging T2 lesions at Months 6 and 12
Adjusted Mean Estimates; Relative risk reduction | 3.650; 35% | 5.592 | <0.0001
Cumulative number of enhancing lesions on T1-weighted images at Months 6 and 12
Adjusted Mean Estimates; Relative risk reduction | 0.905; 45% | 1.639 | <0.0001

16 HOW SUPPLIED/STORAGE AND HANDLING

COPAXONE (glatiramer acetate injection) is a clear, colorless to slightly yellow, sterile, nonpyrogenic solution supplied as:

- 20 mg per mL in a single-dose, prefilled syringe with a white plunger, in individual blister packages supplied in 30-count cartons (NDC 68546-317-30).
- 40 mg per mL in a single-dose, prefilled syringe with a blue plunger, in individual blister packages supplied in 12-count cartons (NDC 68546-325-12).

Some glatiramer acetate products can be administered by an optional compatible autoinjector. Compatible autoinjectors are supplied separately if available, but the availability of compatible autoinjectors may change with time [see Warnings and Precautions (5.7) and Patient Counseling Information (17)].

Store COPAXONE refrigerated at 2°C to 8°C (36°F to 46°F). If needed, the patient may store COPAXONE at room temperature, 15°C to 30°C (59°F to 86°F), for up to one month, but refrigeration is preferred. Avoid exposure to higher temperatures or intense light. Do not freeze COPAXONE. If a COPAXONE syringe freezes, it should be discarded.

17 PATIENT COUNSELING INFORMATION

Advise the patient to read the FDA-approved patient labeling (Medication Guide and Instructions for Use).

Important Administration Instructions

Advise patients with new or existing glatiramer acetate prescriptions to consult their pharmacist or healthcare provider if they would like information about using an optional compatible autoinjector device, if available.

Additionally, advise patients who would like to use an autoinjector for administration, should one be available, that not all available autoinjectors are compatible with all glatiramer acetate products and the availability of compatible autoinjectors may change with time. If you have questions about the availability or compatibility of an autoinjector, contact the manufacturer of the prescribed glatiramer acetate product for more information.

Advise patients that using an optional autoinjector that is not compatible with the glatiramer acetate product may increase the risk for medication errors, such as missing a dose or administration of a partial dose [see Dosage and Administration (2.2), Warnings and Precautions (5.7)].

Anaphylactic Reactions

Advise patients and their caregivers that COPAXONE may cause life-threatening and fatal anaphylactic reactions shortly after injection, and that reactions may occur months to years after initiation of treatment [see Warnings and Precautions (5.1)]. Inform patients and their caregivers about the signs and symptoms specific for anaphylactic reactions, and that signs and symptoms of anaphylactic reactions may overlap with those of immediate post-injection reactions. Instruct them to seek immediate emergency medical care if they experience any signs or symptoms of an anaphylactic reaction [see Warnings and Precautions (5.1, 5.2)]. Patients should be advised to also contact their healthcare provider, and that treatment should be discontinued immediately and permanently if anaphylactic reactions occur.

Immediate Post-Injection Reaction

Advise patients that COPAXONE may cause immediate post-injection reactions, characterized by various symptoms after injection, including flushing, chest pain, palpitations, tachycardia, anxiety, dyspnea, constriction of the throat, and urticaria [see Warnings and Precautions (5.2)]. These symptoms occur within seconds to minutes after injection and are generally transient, self-limited, and do not require specific treatment. Inform patients that these symptoms may occur early or may have their onset several months after the initiation of treatment. A patient may experience one or several episodes of these symptoms.

Advise patients that the symptoms of an immediate post-injection reaction may overlap with those of an anaphylactic reaction. Advise patients to contact their healthcare provider if they experience any signs or symptoms of an immediate post-injection reaction [see Warnings and Precautions (5.1, 5.2)].

Chest Pain

Advise patients that they may experience transient chest pain either as part of the Immediate Post-Injection Reaction or in isolation [see Warnings and Precautions (5.3)]. Inform patients that the pain should be transient. Some patients may experience more than one such episode, usually beginning at least one month after the initiation of treatment. Patients should be advised to seek medical attention if they experience chest pain of unusual duration or intensity.

Lipoatrophy and Skin Necrosis at Injection Site

Advise patients that localized lipoatrophy, and rarely, skin necrosis may occur at injection sites [see Warnings and Precautions (5.4)]. Instruct patients to follow proper injection technique and to rotate injection areas and sites with each injection to minimize these risks.

Hepatic Injury

Advise patients that hepatic injury, including hepatic failure and hepatitis with jaundice, has been reported with the use of COPAXONE. Educate patients about the signs and symptoms of hepatic injury and instruct patients to report them immediately to their healthcare provider [see Warning and Precautions (5.6)].

Pregnancy

Instruct patients that if they are pregnant or plan to become pregnant while taking COPAXONE they should inform their healthcare provider [see Use in Specific Populations (8.1)].

Lactation

Advise patients to notify their healthcare provider if they are breastfeeding or intend to breastfeed during COPAXONE therapy [see Use in Specific Populations (8.2)].

Instructions for Use

Instruct patients to read the COPAXONE Patient Information leaflet carefully. COPAXONE 20 mg per mL and COPAXONE 40 mg per mL are not interchangeable. COPAXONE 20 mg per mL is administered daily and COPAXONE 40 mg per mL is administered three times per week. Caution patients to use aseptic technique. The first injection should be performed under the supervision of a health care professional. Instruct patients to rotate injection areas and sites with each injection. Caution patients against the reuse of needles or syringes. Instruct patients in safe disposal procedures.

Storage Conditions

Advise patients that the recommended storage condition for COPAXONE is refrigeration at 36oF to 46oF (2oC to 8oC). If needed, the patient may store COPAXONE at room temperature, 59oF to 86oF (15oC to 30oC), for up to one month, but refrigeration is preferred. COPAXONE should not be exposed to higher temperatures or intense light. Do not freeze COPAXONE.

Manufactured for: Teva Neuroscience, Inc., Parsippany, NJ 07054
©2025 Teva Neuroscience, Inc.
COP-013

MEDICATION GUIDE

COPAXONE (co-PAX-own)
(glatiramer acetate injection)
for subcutaneous use

Read this Medication Guide before you start using COPAXONE and each time you get a refill. There may be new information. This information does not take the place of talking with your healthcare provider about your medical condition or your treatment.

What is the most important information I should know about COPAXONE?

- Serious allergic reactions (anaphylactic reactions). Serious allergic reactions that may be life-threatening or lead to death may happen any time after you start using COPAXONE. These reactions may happen right after your first dose up to years after starting treatment with COPAXONE, even if you never had an allergic reaction before. Many reactions have happened within 1 hour of using COPAXONE. Some signs and symptoms may be the same as those of an immediate post-injection reaction. See What are the possible side effects of COPAXONE?
  Stop using COPAXONE and get emergency help right away if you have:
  - widespread rash
  - swelling of the face, eyelids, lips, mouth, throat, or tongue
  - sudden shortness of breath, difficulty breathing, or wheezing
  - uncontrolled shaking (convulsions)
  - trouble swallowing or speaking
  - fainting, feeling dizzy or faint

What is COPAXONE?
COPAXONE is a prescription medicine that is used to treat relapsing forms of multiple sclerosis (MS), to include clinically isolated syndrome, relapsing-remitting disease, and active secondary progressive disease, in adults.
It is not known if COPAXONE is safe and effective in children under 18 years of age.

Do not take COPAXONE:

- if you are allergic to glatiramer acetate or mannitol. Serious allergic reactions including life-threatening or anaphylactic reactions that can lead to death have happened. See the end of this leaflet for a complete list of the ingredients in COPAXONE.

Before you use COPAXONE, tell your healthcare provider about all of your medical conditions, including if you:

- are pregnant or plan to become pregnant. Talk to your healthcare provider who will advise if you should take COPAXONE during your pregnancy.
- are breastfeeding or plan to breastfeed. It is not known if COPAXONE passes into your breast milk. Talk to your healthcare provider about the best way to feed your baby while using COPAXONE.

Tell your healthcare provider about all the medicines you take, including prescription and over-the-counter medicines, vitamins, and herbal supplements.
COPAXONE may affect the way other medicines work, and other medicines may affect how COPAXONE works.
Know the medicines you take. Keep a list of your medicines with you to show your healthcare provider and pharmacist when you get a new medicine.

How should I use COPAXONE?

- For detailed instructions, see the Instructions for Use at the end of this leaflet for complete information on how to use COPAXONE.
- Your healthcare provider will tell you how much COPAXONE to use and when to use it.
- COPAXONE is given by injection under your skin (subcutaneously).
- Use COPAXONE exactly as your healthcare provider tells you to use it.
- Since every body type is different, talk with your healthcare provider about the injection areas that are best for you.
- You should receive your first dose of COPAXONE with a healthcare provider or nurse present. This might be at your healthcare provider’s office or with a visiting home health nurse who will teach you how to give your COPAXONE injections.
- Some glatiramer acetate products can be used with an optional compatible autoinjector. Compatible autoinjectors are supplied separately if available, but the availability of compatible autoinjectors may change with time.
  - Check with your healthcare provider when you fill or refill your medicine to make sure the autoinjector you have is meant to be used with your glatiramer acetate product. Not all optional autoinjectors are meant to be used with all glatiramer acetate products. If you use the wrong autoinjector, you might not get the correct dose of your medicine. Contact the manufacturer of your glatiramer acetate product to find out if there is an autoinjector that is meant to be used with your glatiramer acetate product.
- Read your Instructions for Use and talk to your healthcare provider about the best way for you to use COPAXONE.

What are the possible side effects of COPAXONE?
COPAXONE may cause serious side effects, including:

- Immediate Post-Injection Reactions. Serious side effects may happen right after or within minutes after you inject COPAXONE at any time during your course of treatment. Some signs and symptoms may be the same as those of a serious allergic reaction (anaphylaxis). See What is the most important information I should know about COPAXONE? Call a healthcare provider right away if you have any of these immediate post-injection reaction symptoms including:
  - redness to your cheeks or other parts of the body (flushing)
  - chest pain
  - fast heartbeat
  - anxiety
  - breathing problems or tightness in your throat
  - swelling, rash, hives, or itching

If you have symptoms of an immediate post-injection reaction, do not give yourself more injections until a healthcare provider tells you to.

- Chest Pain. You can have chest pain as part of an immediate post-injection reaction or by itself. This type of chest pain usually lasts a few minutes and can begin around 1 month after you start using COPAXONE. Call your healthcare provider right away if you have chest pain while using COPAXONE.
- Damage to your skin. Damage to the fatty tissue just under your skin’s surface (lipoatrophy) and, rarely, death of your skin tissue (necrosis) can happen when you use COPAXONE. Damage to the fatty tissue under your skin can cause a “dent” at the injection site that may not go away. You can reduce your chance of developing these problems by:
  - following your healthcare provider’s instructions for how to use COPAXONE
  - choosing a different injection area each time you use COPAXONE. See Step 4 in the Instructions for Use, “Choose your injection area”.
- Liver problems. Liver problems, including liver failure, can occur with COPAXONE. Call your healthcare provider right away if you have symptoms, such as:
  - nausea
  - loss of appetite
  - tiredness
  - dark colored urine and pale stools
  - yellowing of your skin or the white part of your eye
  - bleeding more easily than normal
  - confusion
  - sleepiness

The most common side effects of COPAXONE are:

- skin problems at your injection site, including:
  - redness
  - pain
  - swelling
  - lumps
  - itching
- rash
- shortness of breath
- flushing (vasodilation)
- chest pain

Tell your healthcare provider if you have any side effect that bothers you or that does not go away.
These are not all the possible side effects of COPAXONE. For more information, ask your healthcare provider or pharmacist.
Call your doctor for medical advice about side effects. You may report side effects to FDA at 1-800-FDA-1088.

How should I store COPAXONE?

- Store COPAXONE in the refrigerator between 36°F to 46°F (2°C to 8°C).
- When you are not able to refrigerate COPAXONE, you may store it for up to 1 month at room temperature between 59°F to 86°F (15°C to 30°C).
- Protect COPAXONE from light or high temperature.
- Do not freeze COPAXONE syringes. If a syringe freezes, throw it away in a sharps disposal container. See Step 13 in the Instructions for Use, “Dispose of your needles and syringes”.

Keep COPAXONE and all medicines out of the reach of children.

General information about the safe and effective use of COPAXONE.
Medicines are sometimes prescribed for purposes other than those listed in a Medication Guide. Do not use COPAXONE for a condition for which it was not prescribed. Do not give COPAXONE to other people, even if they have the same symptoms as you have. It may harm them. You can ask your pharmacist or healthcare provider for information about COPAXONE that is written for health professionals.

What are the ingredients in COPAXONE?
Active ingredient: glatiramer acetate
Inactive ingredients: mannitol
Manufactured for: Teva Neuroscience, Inc., Parsippany, NJ 07054
©2025 Teva Neuroscience, Inc.
COPMG-001
For more information, go to www.copaxone.com or call 1-800-887-8100

This Medication Guide has been approved by the U.S. Food and Drug Administration Revised: January 2025

Instructions for Use

COPAXONE (co-PAX-own)

(glatiramer acetate injection)

for subcutaneous use

For subcutaneous injection only.

Do not inject COPAXONE in your veins (intravenously).

Do not re-use your COPAXONE prefilled syringes.

Do not share your COPAXONE prefilled syringes with another person. You may give another person an infection or get an infection from them.

You should receive your first dose of COPAXONE with a healthcare provider or nurse present. This might be at your healthcare provider’s office or with a visiting home health nurse who will show you how to give your own injections.

COPAXONE comes in either a 20 mg Prefilled Syringe with needle attached or a 40 mg Prefilled Syringe with needle attached. How often a dose is given depends on the product strength that is prescribed. Your healthcare provider will prescribe the correct dose for you.

If you plan to use your glatiramer acetate product with an autoinjector, ask your healthcare provider or pharmacist to make sure that your autoinjector is meant to be used with your glatiramer acetate product. If you use an autoinjector that is not meant to be used with your glatiramer acetate product, you might not get the correct dose of your medicine.

Instructions for Using Your COPAXONE 20 mg Prefilled Syringe:

- COPAXONE 20 mg is injected 1 time each day, in the fatty layer under your skin (subcutaneously).
- Each COPAXONE 20 mg prefilled syringe is for single use (1 time use) only.
- The COPAXONE 20 mg dose is packaged in boxes of 30 prefilled syringes with needles attached. COPAXONE 20 mg prefilled syringes have white plungers.

Instructions for Using Your COPAXONE 40 mg Prefilled Syringe:

- COPAXONE 40 mg is injected 3 times each week, in the fatty layer under your skin (subcutaneously).
- COPAXONE 40 mg should be given on the same 3 days each week, if possible, for example, Monday, Wednesday, and Friday. Give your COPAXONE injections at least 48 hours (2 days) apart.
- Each COPAXONE 40 mg prefilled syringe is for single use (1 time use) only.
- The COPAXONE 40 mg dose is packaged in boxes of 12 prefilled syringes with needles attached. COPAXONE 40 mg prefilled syringes have blue plungers.

How do I inject COPAXONE?

Step 1: Gather the supplies you will need to inject COPAXONE. See Figure A.

- 1 blister pack with a COPAXONE Prefilled Syringe with needle attached
- Alcohol wipe (not supplied)
- Dry cotton ball (not supplied)
- A place to record your injections, like a notebook (not supplied)
- Sharps disposal container (not supplied). See Step 13 below, “Dispose of your needles and syringes”.

Figure A

Step 2: Remove only 1 blister pack from the COPAXONE prefilled syringe carton. See Figure B.

Figure B

- Place the supplies you will need on a clean, flat surface in a well-lit area.
- After you remove 1 blister pack from the carton, keep all unused syringes in the carton and store them in the refrigerator.
- Let the blister pack, with the syringe inside, warm to room temperature for about 20 minutes.
- Wash your hands. Be careful not to touch your face or hair after washing your hands.

Step 3: Look closely at your COPAXONE prefilled syringe.

- There may be small air bubbles in the syringe. Do not try to push the air bubble from the syringe before giving your injection so you do not lose any medicine.
- Check the liquid medicine in the syringe before you give your injection. The liquid in the syringe should look clear, and colorless, and may look slightly yellow. If the liquid is cloudy or contains any particles, do not use the syringe and throw it away in a sharps disposal container. See Step 13 below, “Dispose of your needles and syringes.”

Step 4: Choose your injection area. See Figure C.

See the injection areas you should use on your body. Talk with your healthcare provider about the injection areas that are best for you.

- The possible injection areas on your body include (See Figure C):
  - your stomach area (abdomen) around the belly button
  - the back of your upper arms
  - upper hips (below your waist)
  - your thighs (above your knees)

Figure C

- For each COPAXONE dose, choose a different injection area from 1 of the areas shown above. See Figure C.
- Do not stick the needle in the same place (site) more than 1 time each week. Each injection area contains multiple injection sites for you to choose from. Avoid injecting in the same site over and over again.
- Keep a record of the sites where you give your injection each day so you will remember where you already injected.

Step 5: Prepare to give your injection.

- There are some injection areas on your body that are hard to reach (like the back of your arm). You may need help from someone who has been instructed on how to give your injection if you cannot reach certain injection areas.
- Do not inject in sites where the skin has scarring or “dents”. Using scarred or dented skin for your injections may make your skin worse.

Step 6: Clean your injection site.

- Clean the injection site using the alcohol wipe and allow your skin to air dry. See Figure D.

Figure D

Step 7: Pick up the syringe with 1 hand and hold it like a pencil. Remove the needle cover with your other hand and set it aside. See Figure E.

Figure E

Step 8: Pinch about a 2 inch fold of skin between your thumb and index finger. See Figure F.

Figure F

Step 9: Giving your injection.

- Rest the heel of your hand holding the syringe against your skin at the injection site. Insert the needle at a 90 degree angle straight into your skin. See Figure G.

Figure G

- When the needle is all the way into your skin, release the fold of skin. See Figure H.

Figure H

Step 10: Give your COPAXONE injection.

To inject the medicine, hold the syringe steady and slowly push down the plunger. See Figure I.

Figure I

Step 11: Remove the needle.

After you have injected all of the medicine, pull the needle straight out. See Figure J.

Figure J

Step 12: Use a clean, dry cotton ball to gently press on the injection site for a few seconds. Do not rub the injection site or re-use the needle or syringe. See Figure K.

Figure K

Step 13: Dispose of your needles and syringes.

- Put your used needles and syringes in a FDA-cleared sharps disposal container right away after use. Do not throw away (dispose of) loose needles and syringes in your household trash.
- If you do not have a FDA-cleared sharps disposal container, you may use a household container that is:
  - made of a heavy-duty plastic,
  - can be closed with a tight-fitting, puncture-resistant lid, without sharps being able to come out,
  - upright and stable during use,
  - leak-resistant, and
  - properly labeled to warn of hazardous waste inside the container.
- When your sharps disposal container is almost full, you will need to follow your community guidelines for the right way to dispose of your sharps disposal container. There may be state or local laws about how you should throw away used needles and syringes. For more information about safe sharps disposal, and for specific information about sharps disposal in the state that you live in, go to the FDA’s website at: http://www.fda.gov/safesharpsdisposal.
- Do not dispose of your used sharps disposal container in your household trash unless your community guidelines permit this. Do not recycle your used sharps disposal container.

Figure L

This Instructions for Use has been approved by the U.S. Food and Drug Administration.

Manufactured for: Teva Neuroscience, Inc., Parsippany, NJ 07054
©2023 Teva Neuroscience, Inc.

COPIFU-008
Revised: November 2023

Package/Label Display Panel, 20 mg/mL

NDC 68546-317-30
ONCE DAILY
COPAXONE® (glatiramer acetate injection) 20 mg/mL
Rx Only
30 Single-Dose Pre-Filled Syringes
Each pre-filled syringe contains 1 mL COPAXONE® solution of: glatiramer acetate 20 mg; mannitol 40 mg (inactive ingredient)
FOR SUBCUTANEOUS INJECTION ONLY
Manufactured for: Teva Neuroscience, Inc.,
Parsippany, NJ 07054 Product of Israel
teva

Package/Label Display Panel,40 mg/mL

NDC 68546-325-12
THREE TIMES A WEEK
COPAXONE® (glatiramer acetate injection) 40 mg/mL
Rx Only
12 Single-Dose Pre-Filled Syringes
Each pre-filled syringe contains 1 mL COPAXONE® solution of: glatiramer acetate 40 mg; mannitol 40 mg (inactive ingredient)
FOR SUBCUTANEOUS INJECTION ONLY
Manufactured for: Teva Neuroscience, Inc.,
Parsippany, NJ 07054 Product of Israel
teva